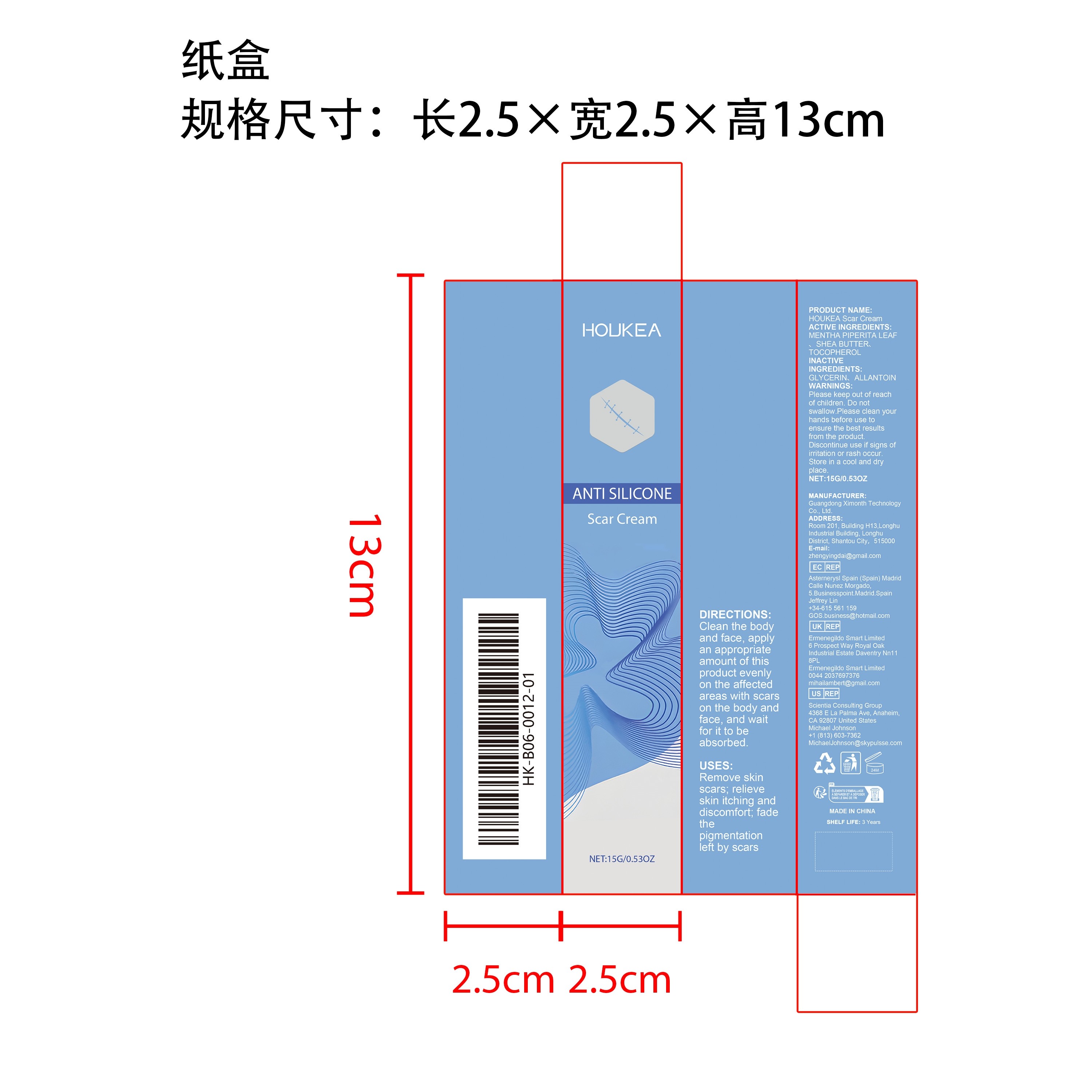 DRUG LABEL: HOUKEA Scar Cream
NDC: 84660-090 | Form: CREAM
Manufacturer: Guangdong Ximonth Technology Co., Ltd.
Category: otc | Type: HUMAN OTC DRUG LABEL
Date: 20241029

ACTIVE INGREDIENTS: TOCOPHEROL 2.25 g/15 g; MENTHA PIPERITA LEAF 4.5 g/15 g; SHEA BUTTER 1.5 g/15 g
INACTIVE INGREDIENTS: GLYCERIN 2.25 g/15 g; ALLANTOIN 4.5 g/15 g

ACTIVE INGREDIENTS

MENTHA PIPERITA LEAF、SHEA BUTTER、TOCOPHEROL

PURPOSE

Remove skin scars; relieve skin itching and discomfort; fade the pigmentation left by scars

USES

Clean the body and face, apply an appropriate amount of this product evenly on the affected areas with scars on the body and face, and wait for it to be absorbed.

WARNINGS

Please keep out of reach of children. Do not swallow.Please clean your hands before use to ensure the best results from the product. Discontinue use if signs of irritation or rash occur. Store in a cool and dry place.

STOP USE

Discontinue use if signs of irritation or rash occur.

DO NOT USE

Discontinue use if signs of irritation or rash occur.

KEEP OUT OF REACH OF CHILDREN

Please keep out of reach of children. Do not swallow.

STORAGE AND HANDLING

Store in a cool and dry place.

INACTIVE INGREDIENT

GLYCERIN、ALLANTOIN